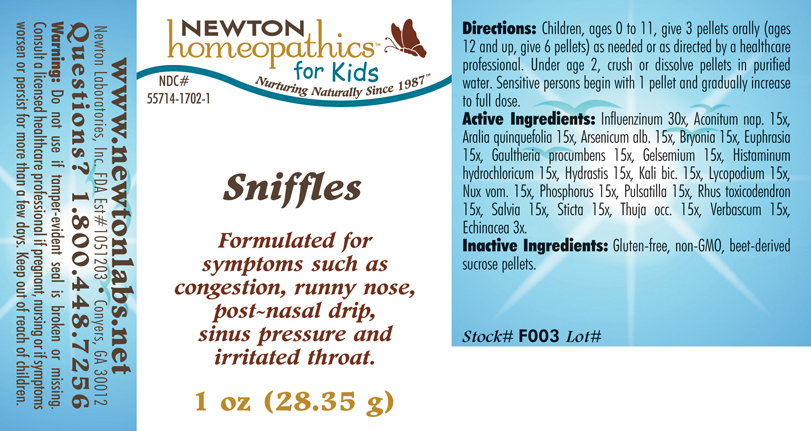 DRUG LABEL: Sniffles 
NDC: 55714-1702 | Form: PELLET
Manufacturer: Newton Laboratories, Inc.
Category: homeopathic | Type: HUMAN OTC DRUG LABEL
Date: 20110301

ACTIVE INGREDIENTS: Influenza A Virus 30 [hp_X]/1 g; Aconitum Napellus 15 [hp_X]/1 g; American Ginseng 15 [hp_X]/1 g; Arsenic Trioxide 15 [hp_X]/1 g; Bryonia Alba Root 15 [hp_X]/1 g; Euphrasia Stricta 15 [hp_X]/1 g; Gaultheria Procumbens Top 15 [hp_X]/1 g; Gelsemium Sempervirens Root 15 [hp_X]/1 g; Histamine Dihydrochloride 15 [hp_X]/1 g; Goldenseal 15 [hp_X]/1 g; Potassium Dichromate 15 [hp_X]/1 g; Lycopodium Clavatum Spore 15 [hp_X]/1 g; Strychnos Nux-vomica Seed 15 [hp_X]/1 g; Phosphorus 15 [hp_X]/1 g; Pulsatilla Vulgaris 15 [hp_X]/1 g; Toxicodendron Pubescens Leaf 15 [hp_X]/1 g; Sage 15 [hp_X]/1 g; Lobaria Pulmonaria 15 [hp_X]/1 g; Thuja Occidentalis Leafy Twig 15 [hp_X]/1 g; Verbascum Thapsus 15 [hp_X]/1 g; Echinacea, Unspecified 3 [hp_X]/1 g; Influenza B Virus 30 [hp_X]/1 g
INACTIVE INGREDIENTS: Sucrose

Sniffles

INDICATIONS & USAGE SECTION

Sniffles Formulated for symptoms such as congestion, runny nose, post-nasal drip, sinus pressure and irritated throat.

DOSAGE & ADMINISTRATION SECTION

Directions: Children, ages 0 to 11, give 3 pellets orally (ages 12 and up, give 6 pellets) as needed or as directed by a healthcare professional. Under age 2, crush or dissolve pellets in purified water. Sensitive persons begin with 1 pellet and gradually increase to full dose.

OTC - ACTIVE INGREDIENT SECTION

Influenzinum 30x, Aconitum nap. 15x ,Aralia quinquefolia 15x, Arsenicum alb. 15x, Bryonia 15x, Euphrasia 15x, Gaultheria procumbens 15x, Gelsemium 15x, Histaminum hydrochloricum 15x, Hydrastis 15x, Kali bic. 15x, Lycopodium 15x, Nux vom. 15x, Phosphorus 15x, Pulsatilla 15x, Rhus toxicodendron 15x, Salvia 15x, Sticta 15x, Thuja occ. 15x, Verbascum 15x, Echinacea 3x.

OTC - PURPOSE SECTION

Formulated for symptoms such as congestion, runny nose, post-nasal drip, sinus pressure and irritated throat.

INACTIVE INGREDIENT SECTION

Inactive Ingredients: Gluten-free, non-GMO, beet-derived sucrose pellets.

QUESTIONS SECTION

www.newtonlabs.net Newton Laboratories, Inc. FDA Est # 1051203 - Conyers, GA 30012
Questions? 1.800.448.7256

WARNINGS SECTION

Warning: Do not use if tamper - evident seal is broken or missing. Consult a licensed healthcare professional if pregnant, nursing or if symptoms worsen or persist for more than a few days. Keep out of reach of children.

OTC - PREGNANCY OR BREAST FEEDING SECTION

Consult a licensed healthcare professional if pregnant, nursing or if symptoms worsen or persist for more than a few days.

OTC - KEEP OUT OF REACH OF CHILDREN SECTION

Keep out of reach of children.